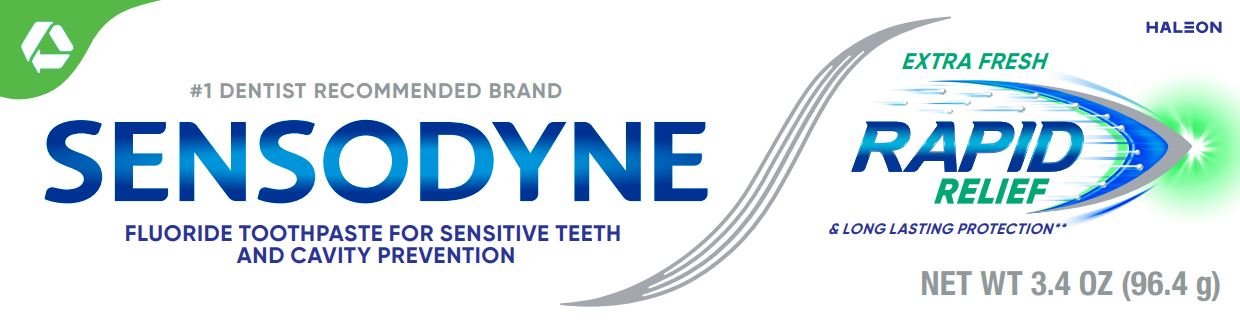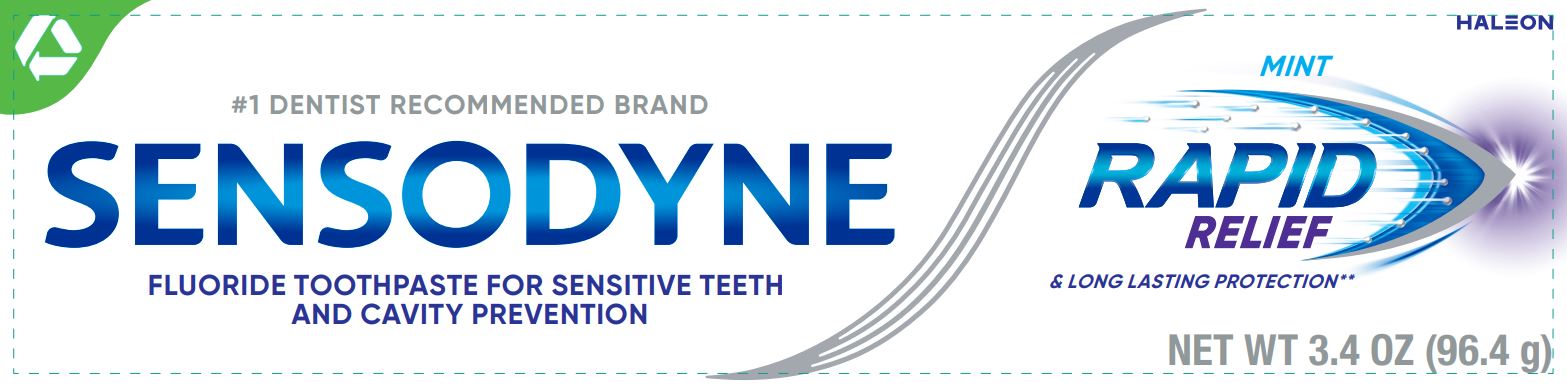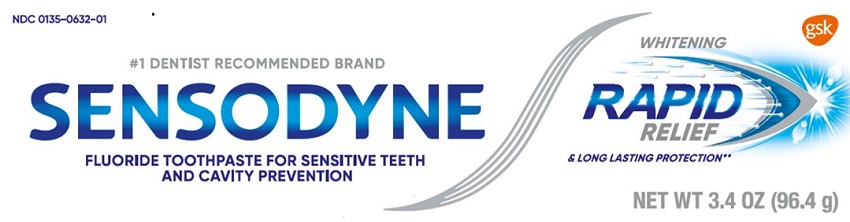 DRUG LABEL: SENSODYNE

NDC: 0135-0622 | Form: PASTE
Manufacturer: Haleon US Holdings LLC
Category: otc | Type: HUMAN OTC DRUG LABEL
Date: 20240306

ACTIVE INGREDIENTS: STANNOUS FLUORIDE 1.1 mg/1 g
INACTIVE INGREDIENTS: GLYCERIN; POLYETHYLENE GLYCOL 400; HYDRATED SILICA; SODIUM TRIPOLYPHOSPHATE ANHYDROUS; SODIUM LAURYL SULFATE; TITANIUM DIOXIDE; COCAMIDOPROPYL BETAINE; SACCHARIN SODIUM

Drug Facts

Active ingredient

Stannous fluoride 0.454% (0.15% w/v fluoride ion)

Purposes

Anticavity

Antihypersensitivity

Uses

- aids in the prevention of dental cavities.
- builds increasing protection against painful sensitivity of the teeth to cold, heat, acids, sweets or contact.

Warnings

Stop use and ask a dentist if

- the problem persists or worsens. Sensitive teeth may indicate a serious problem that may need prompt care by a dentist.
- pain/sensitivity still persists after 4 weeks of use.

Keep out of reach of children.

If more than used for brushing is accidentally swallowed, get medical help or contact a Poison Control Center right away.

Directions

- adults and children 12 years of age and older:
  - apply at least a 1-inch strip of the product onto a soft bristle toothbrush.
  - brush teeth thoroughly for at least 1 minute twice a day (morning and evening), and not more than 3 times a day, or as recommended by a dentist or doctor. Make sure to brush all sensitive areas of the teeth. Minimize swallowing. Spit out after brushing.
- children under 12 years of age:Consult a dentist or doctor.

Other information

- products containing stannous fluoride may produce surface staining of the teeth. Adequate toothbrushing may prevent these stains which are not harmful or permanent and may be removed by your dentist.
- this product is specifically formulated to help prevent staining
- do not store above 30°C (86°F)

Inactive ingredients (Extra Fresh)

glycerin, PEG-8, hydrated silica, pentasodium triphosphate, flavor, sodium lauryl sulfate, titanium dioxide, polyacrylic acid, cocamidopropyl betaine, sodium saccharin

Inactive ingredients (Mint)

glycerin, PEG-8, hydrated silica, pentasodium triphosphate, flavor, sodium lauryl sulfate, titanium dioxide, polyacrylic acid, sodium saccharin, cocamidopropyl betaine

Inactive Ingredients (Whitening)

glycerin, PEG-8, hydrated silica, pentasodium triphosphate, flavor, sodium lauryl sulfate, titanium dioxide, polyacrylic acid, sodium saccharin, cocamidopropyl betaine

Questions or comments?

1-866-844-2797

Additional Information

ALWAYS FOLLOW THE LABEL

SENSODYNE RAPIDRELIEF

What is tooth sensitivity?

Sensitivity occurs when the dentin underneath tooth enamel becomes exposed. When exposed dentin comes into contact with hot or cold, sweet or sour, or even your toothbrush, it can trigger the nerve causing a short, sharp pain.

CAUSE OF SENSITIVITY PAIN

TINY HOLES IN DENTIN

FAST ACTING FORMULA

QUICKLY CREATES A BARRIER

FAST RELIEF FROM PAIN*

Fast RELIEF* and Long lasting Protection**

Sensodyne Rapid Relief is clinically proven for fast relief of sensitivity pain.

Its formula quickly creates a barrier over sensitive areas of your teeth to provide fast relief, and to help stop the pain from coming back. With twice daily brushing, it builds ongoing protection from the pain of sensitive teeth. It also helps whiten enamel and prevents staining.

*significant pain relief in 3 days

**with twice daily brushing

Trademarks are owned by or licensed to the Haleon group of companies.

©2023 Haleon group of companies or its licensor.

Distributed by: Haleon, Warren, NJ 07059

Pat. Info www.productpats.com

Principal Display Panel

#1 DENTIST RECOMMENDED BRAND

SENSODYNE

FLUORIDE TOOTHPASTE FOR SENSITIVE TEETH

AND CAVITY PREVENTION

EXTRA FRESH

RAPID RELIEF

& LONG LASTING PROTECTION**

NET WT 3.4 OZ (96.4 g)

62000000207034

Principal Display Panel

#1 DENTIST RECOMMENDED BRAND

SENSODYNE

FLUORIDE TOOTHPASTE FOR SENSITIVE TEETH

AND CAVITY PREVENTION

MINT

RAPID RELIEF

& LONG LASTING PROTECTION**

NET WT 3.4 OZ (96.4 g)

62000000207014

Principal Display Panel

NDC 0135-0632-01

#1 DENTIST RECOMMENDED BRAND

SENSODYNE

FLUORIDE TOOTHPASTE FOR SENSITIVE TEETH

AND CAVITY PREVENTION

WHITENING

RAPID RELIEF

& LONG LASTING PROTECTION**

NET WT 3.4 OZ (96.4 g)

62000000057071 Carton